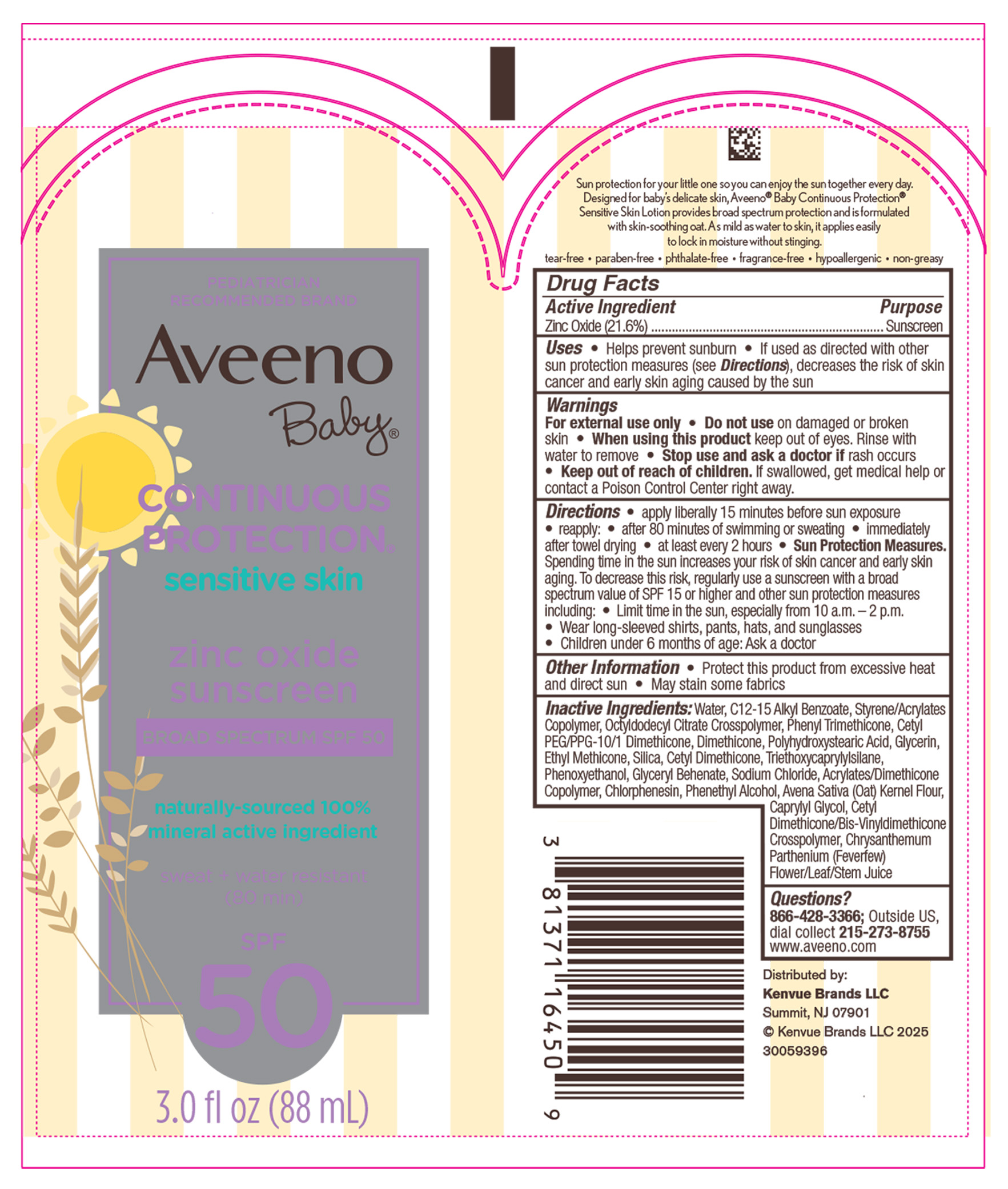 DRUG LABEL: Aveeno Baby continuous protection sensitive skin
NDC: 69968-0304 | Form: LOTION
Manufacturer: Kenvue Brands LLC
Category: otc | Type: HUMAN OTC DRUG LABEL
Date: 20250304

ACTIVE INGREDIENTS: ZINC OXIDE 216 mg/1 mL
INACTIVE INGREDIENTS: WATER; ALKYL (C12-15) BENZOATE; PHENYL TRIMETHICONE; CETYL PEG/PPG-10/1 DIMETHICONE (HLB 5); DIMETHICONE; POLYHYDROXYSTEARIC ACID (2300 MW); GLYCERIN; ETHYL METHICONE (8 MPA.S); SILICON DIOXIDE; CETYL DIMETHICONE 25; TRIETHOXYCAPRYLYLSILANE; PHENYLETHYL ALCOHOL; OATMEAL; CAPRYLYL GLYCOL; GLYCERYL DIBEHENATE; SODIUM CHLORIDE; CHLORPHENESIN; PHENOXYETHANOL; FEVERFEW; BUTYL METHACRYLATE/METHYL METHACRYLATE/METHACRYLIC ACID/STYRENE CROSSPOLYMER; OCTYLDODECYL CITRATE CROSSPOLYMER; CETYL DIMETHICONE/BIS-VINYLDIMETHICONE CROSSPOLYMER

Aveeno Baby® CONTINUOUS PROTECTION® sensitive skin sunscreen
BROAD SPECTRUM SPF 50

Drug Facts

Active Ingredient

Zinc Oxide 21.6%

Purpose

Sunscreen

Uses

- Helps prevent sunburn
- If used as directed with other sun protection measures (see Directions), decreases the risk of skin cancer and early skin aging caused by the sun

Warnings

For external use only

- Do not use on damaged or broken skin

- When using this product keep out of eyes. Rinse with water to remove

- Stop use and ask a doctor if rash occurs

- Keep out of reach of children. If swallowed, get medical help or contact a Poison Control Center right away.

Directions

- apply liberally 15 minutes before sun exposure
- reapply:
  - after 80 minutes of swimming or sweating
  - immediately after towel drying
  - at least every 2 hours
- Sun Protection Measures. Spending time in the sun increases your risk of skin cancer and early skin aging. To decrease this risk, regularly use a sunscreen with a broad spectrum value of SPF 15 or higher and other sun protection measures including:
  - Limit time in the sun, especially from 10 a.m.-2 p.m.
  - Wear long-sleeved shirts, pants, hats, and sunglasses
- Children under 6 months of age: Ask a doctor

Other Information

- Protect this product from excessive heat and direct sun
- May stain some fabrics

Inactive Ingredients

Water, C 12-15 Alkyl Benzoate, Styrene/Acrylates Copolymer, Octyldodecyl Citrate Crosspolymer, Phenyl Trimethicone, Cetyl PEG/PPG-10/1 Dimethicone, Dimethicone, Polyhydroxystearic Acid, Glycerin, Ethyl Methicone, Silica, Cetyl Dimethicone, Triethoxycaprylylsilane, Phenoxyethanol, Glyceryl Behenate, Sodium Chloride, Acrylates/Dimethicone Copolymer, Chlorphenesin, Phenethyl Alcohol, Avena Sativa (Oat) Kernel Flour, Caprylyl Glycol, Cetyl Dimethicone/Bis-Vinyldimethicone Crosspolymer, Chrysanthemum Parthenium (Feverfew)Flower/Leaf/Stem Juice

Questions

866-428-3366; Outside US , dial collect 215-273-8755 www.aveeno.com

Distributed by:
Kenvue Brands LLC
Summit, NJ 07901

PRINCIPAL DISPLAY PANEL - 207 mL Tube Label

PEDIATRICIAN
RECOMMENDED BRAND
Aveeno
Baby ®
CONTINUOUS
PROTECTION®
sensitive skin
zinc oxide
sunscreen
BROAD SPECTRUM SPF 50
naturally-sourced 100%
mineral active ingredient
sweat + water resistant
(80 min)
SPF
50
3.0 fl oz (88 mL)